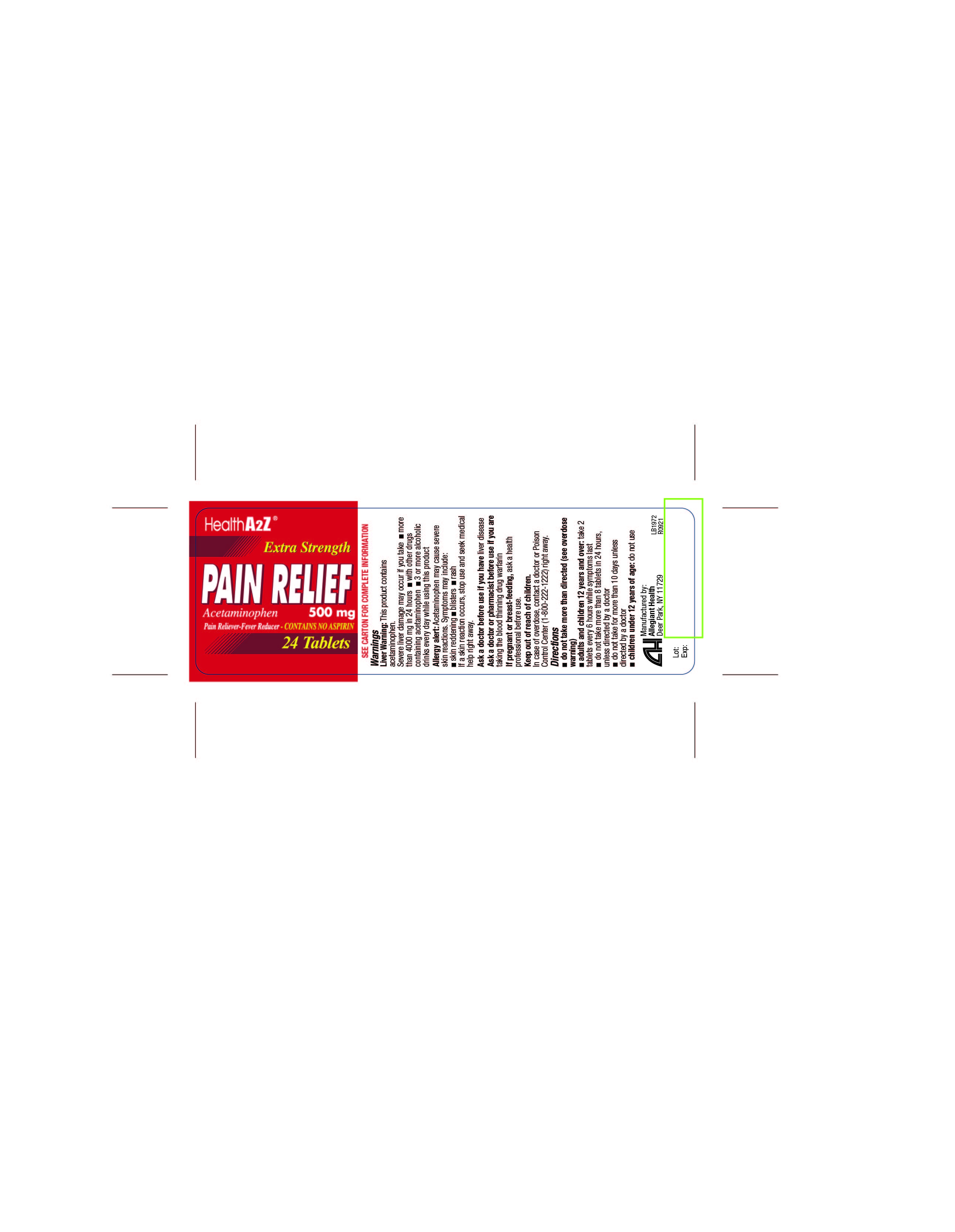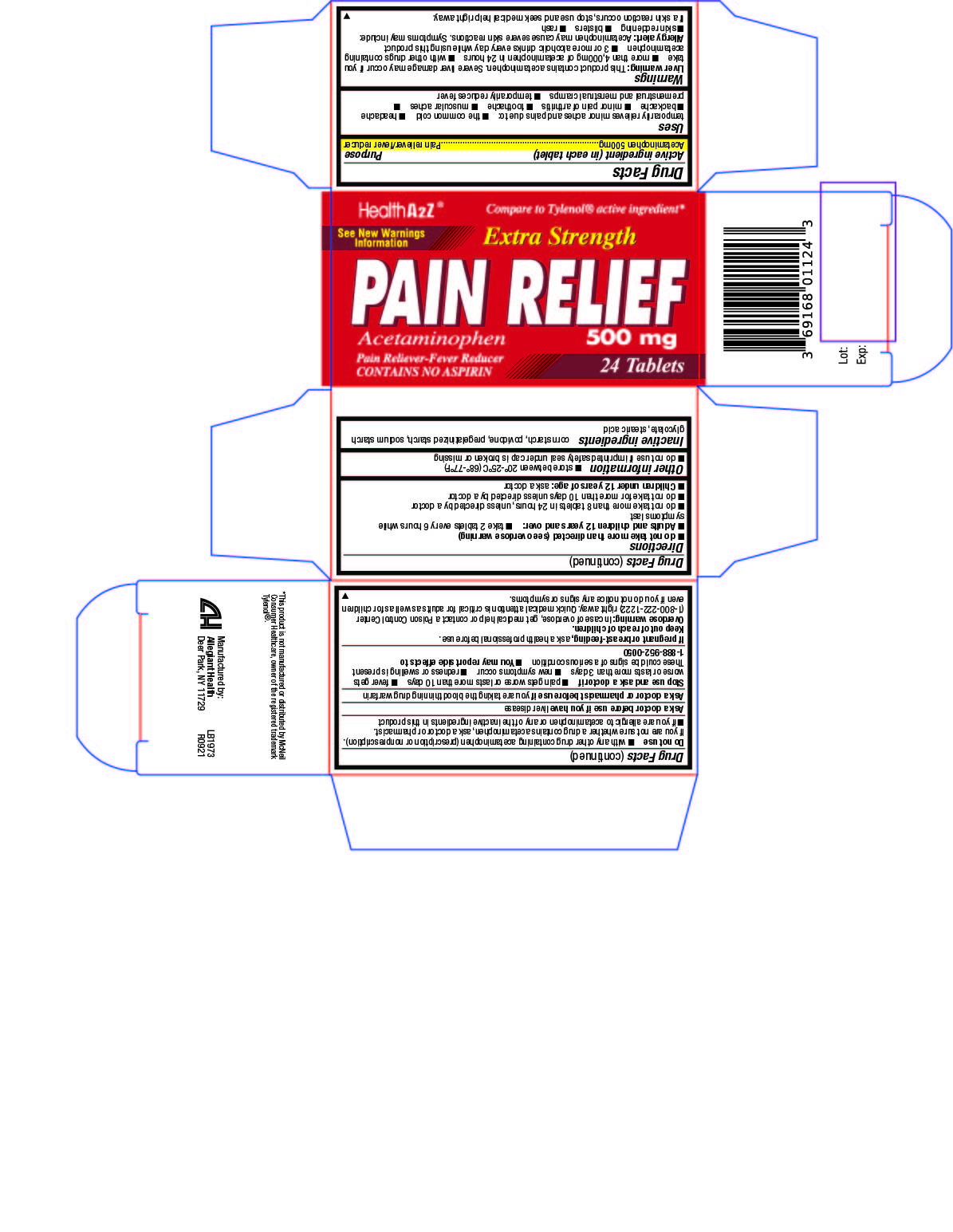 DRUG LABEL: Acetaminophen 500mg
NDC: 69168-011 | Form: TABLET
Manufacturer: Allegiant Health
Category: otc | Type: HUMAN OTC DRUG LABEL
Date: 20190108

ACTIVE INGREDIENTS: Acetaminophen 500 mg/1 1
INACTIVE INGREDIENTS: STARCH, CORN; POVIDONE; SODIUM STARCH GLYCOLATE TYPE A CORN; STEARIC ACID

Drug Facts

Active Ingredient (in each tablet)

Acetaminophen 500 mg

Purpose

Pain reliever/fever reducer

Uses

temporary relief of minor aches and pains associated with

- common cold
- headache
- toothache
- muscular aches
- backache
- arthritis
- menstrual cramps
- temporarily reduces fever

Warnings

Liver Warning: This product contains acetaminophen. Severe liver damage may occur if you take

- more than 4000 mg of acetaminophen in 24 hours
- with other drugs containing acetaminophen
- 3 or more alcoholic drinks every day while using this product

Allergy alert: Acetaminophen may cause severe skin reactions. Symptoms may include:

- skin reddening
- blisters
- rash

If a skin reaction occurs, stop use and seek medical help right away.

Do not use

- if you are allergic to acetaminophen
- with any other drug containing acetaminophen (prescription or nonprescription).

If you are not sure whether a drug contains acetaminophen, ask a doctor or pharmacist.

Ask a doctor before use if you have

liver disease

Ask a doctor or pharmacist before use if you are

taking the blood thinning drug warfarin.

Stop use and ask a doctor if

- symptoms do not improve
- pain gets worse or lasts for more than 10 days
- pain get worse or lasts more than 5 days in children under 12 years
- fever gets worse or lasts for more than 3 days
- new symptoms occur
- redness or swelling is present
- a rare sensitivity reaction occurs
- You may report side effects to 1-888-952-0050

If pregnant or breast-feeding

ask a health professional before use.

Keep out of reach of children

In case of accidental overdose, contact a doctor or Poison Control Center (1-800-222-1222) right away. Quick medical attention is critical for adults as well as for children even if you do not notice any signs or symptoms.

Directions

- do not use more than directed (see overdose warning)
- adults and children 12 years and over: take 2 tablets every 4 to 6 hours. Do not take more than 8 tablets in 24 hours.
- Do not use more than 10 days unless directed by a doctor
- children under 12 years of age: do not use this extra strength product; this will provide more than the recommended dose (overdose) and could cause serious health problems.

Other information

- store between 20°-25°C (68°-77°F)
- do not use if imprinted safety seal under cap is broken or missing

Inactive ingredients

corn starch, povidone, pregelatinized starch, sodium starch glycolate, stearic acid

Principal Display Panel

Pain Relief
Pain Relief